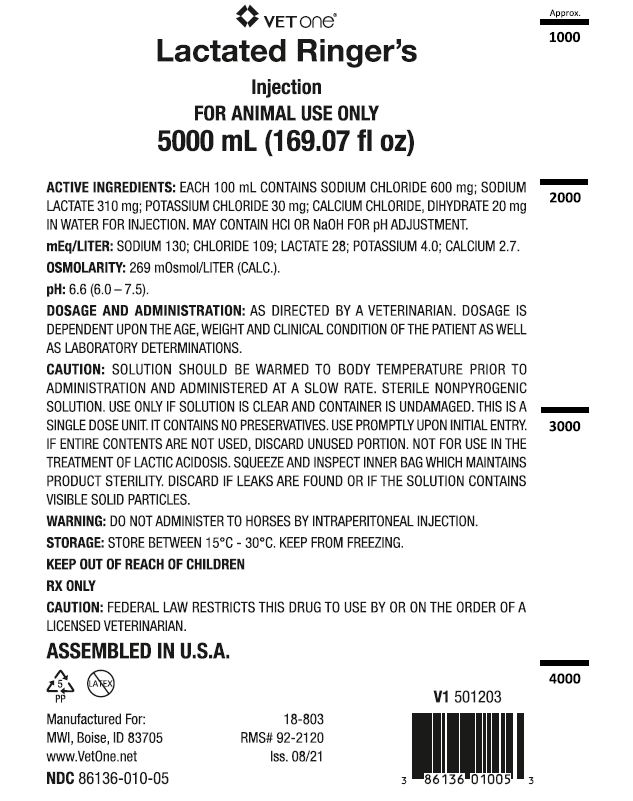 DRUG LABEL: Lactated Ringers
NDC: 86136-010 | Form: INJECTION, SOLUTION
Manufacturer: MWI (VetOne)
Category: animal | Type: PRESCRIPTION ANIMAL DRUG LABEL
Date: 20221208

ACTIVE INGREDIENTS: SODIUM CHLORIDE 600 mg/100 mL; SODIUM LACTATE 310 mg/100 mL; POTASSIUM CHLORIDE 30 mg/100 mL; CALCIUM CHLORIDE 20 mg/100 mL

Lactated Ringers

DOSAGE AND ADMINISTRATION:

As directed by a veterinarian. Dosage is dependent upon the age, weight and clinical condition of the patient as well as laboratory determinations.

INFORMATION FOR OWNERS/CAREGIVERS

Assembled in U.S.A.

Manufactured for:

MWI, Boise, ID 83705
www.VetOne.net

V1 501203

5000 mL (169.07 fl oz)

18-803

RMS# 92-2120

Iss. 08/21

VETERINARY INDICATIONS

For animal use only

Keep out of reach of children.

RX Only

CAUTION:

Federal law restricts this drug to use by or on the order of a licensed veterinarian.

Active Ingredients:

Each 100 mL contains Sodium Chloride 600 mg; Sodium Lactate 310 mg; Potassium Chloride 30 mg; Calcium Chloride, Dihydrate 20 mg in water for Injection. May contain HCl or NaOH for pH adjustment.

mEq/liter: Sodium 130; Chloride 109; Lactate 28; Potassium 4.0; Calcium 2.7.

Osmolarity: 269 mOsml/liter (calc).

pH: 6.6 (6.0 - 7.5).

CAUTION:

Solution should be warmed to body temperature prior to administration and administered at a slow rate. Sterile nonpyrogenic solution. Use only if solution is clear and container is undamaged. This is a single dose unit. It contains no preservatives. Use promptly upon initial entry. If entire contents are not used, discard unused portion. Not for use in the treatment of lactic acidoses. Squeeze and inspect inner bag which maintains product sterility. Discard if leaks are found or if the solution contains visible solid particles.

WARNING:

Do not administer to horses by intraperitoneal injection.

STORAGE:

Store between 15°C - 30°C. Keep from freezing.